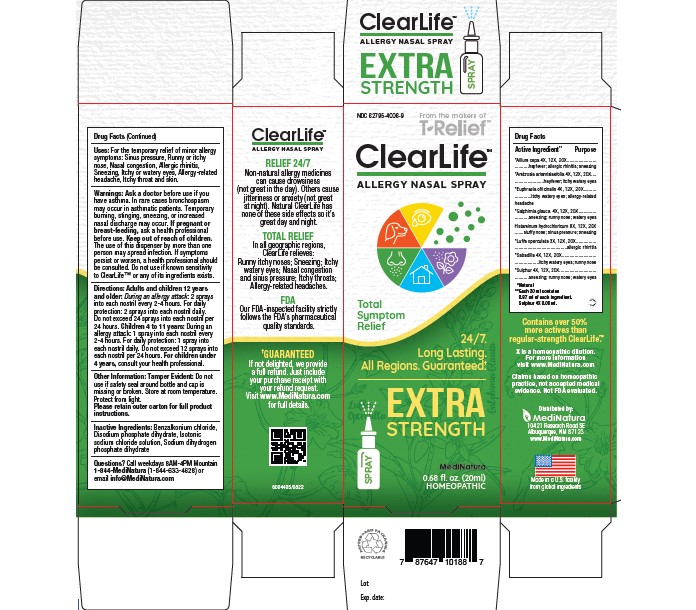 DRUG LABEL: Clearlife Extra Strength
NDC: 62795-4006 | Form: SPRAY
Manufacturer: MediNatura Inc.
Category: homeopathic | Type: HUMAN OTC DRUG LABEL
Date: 20230306

ACTIVE INGREDIENTS: ONION 4 [hp_X]/20 mL; GALPHIMIA GLAUCA FLOWERING TOP 4 [hp_X]/20 mL; HISTAMINE DIHYDROCHLORIDE 8 [hp_X]/20 mL; LUFFA OPERCULATA FRUIT 3 [hp_X]/20 mL; SULFUR 4 [hp_X]/20 mL; AMBROSIA ARTEMISIIFOLIA WHOLE 4 [hp_X]/20 mL; EUPHRASIA STRICTA 4 [hp_X]/20 mL; SCHOENOCAULON OFFICINALE SEED 4 [hp_X]/20 mL
INACTIVE INGREDIENTS: BENZALKONIUM CHLORIDE; SODIUM PHOSPHATE, DIBASIC, DIHYDRATE; SODIUM PHOSPHATE, MONOBASIC, DIHYDRATE; SODIUM CHLORIDE

Clearlife Extra Strength

ACTIVE INGREDIENTS

*Allium cepa 4X, 12X, 20X, Ambrosia Artemisiaefolia 4X,12X, 20X, Euphrasia Officinalis 4X, 12X, 20X, *Galphimia glauca 4X, 12X, 20X *Histaminum hydrochloricum 8X,12X, 20X, *Luffa operculate 3X,12X, 20X, Sabadilla 4X, 12X, 20X, *Sulphur 4X, 12X, 20X
*Natural Ingredients.

PURPOSE

Relieves:
• Runny or itchy Nose
• Sneezing
• Nasal Congestion
• Sinus pressure
• Allergic rhinitis
• itchy or watery eyes
• Allergic related headache

KEEP OUT OF REACH OF CHILDREN

INDICATIONS AND USAGE

For the temporary relief of minor allergy symptoms:Sinus pressure, Runny or itchy nose, Nasal congestion, Allergic rhinitis, sneezing, itchy or watery eyes, Allergic related headache, itchy throat or skin.

WARNINGS

Ask a doctor before use if you have asthma. In rare cases broncho-spasm may occur in asthmatic patients. Temporary burning, stinging, sneezing or increased nasal discharge may occur. If pregnant or breast-feeding, ask a healthcare professional before use. Keep out of reach of children. The use of this dispenser by more than one person may spread infection. If symptoms persist or worsen, a healthcare professional should be consulted. Do not use if known sensitivity to ClearLife™ or any of its ingredients exists.

Directions:

Adults and children 12 years and older: During an allergy attack: 2 sprays into each nostril every 2-4 hours. For daily protection:2 sprays into each nostril daily. Do not exceed 24 sprays in each nostril per 24 hours.
Children 4 to 11 years: During an allergy attack:1 spray into each nostril every 2 to 4 hours. For daily protection 1 spray into each nostril daily. Do not exceed 12 sprays in each nostril per 24 hours.

For children under 4 years, consult your health professional.

INACTIVE INGREDIENTS

Benzalkonium chloride, Disodium phosphate dihydrate, Isotonic sodiumchloride solution, Sodium dihydrogen phosphate dihydrate

PACKAGE LABEL

Add image transcription here...